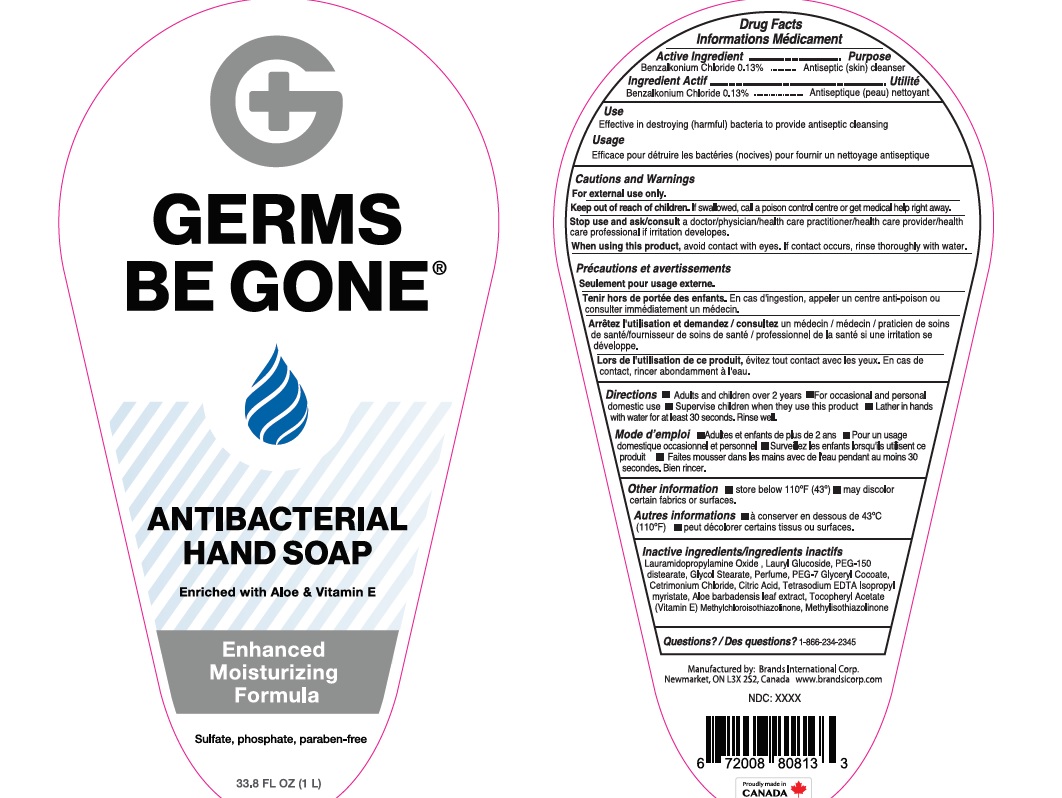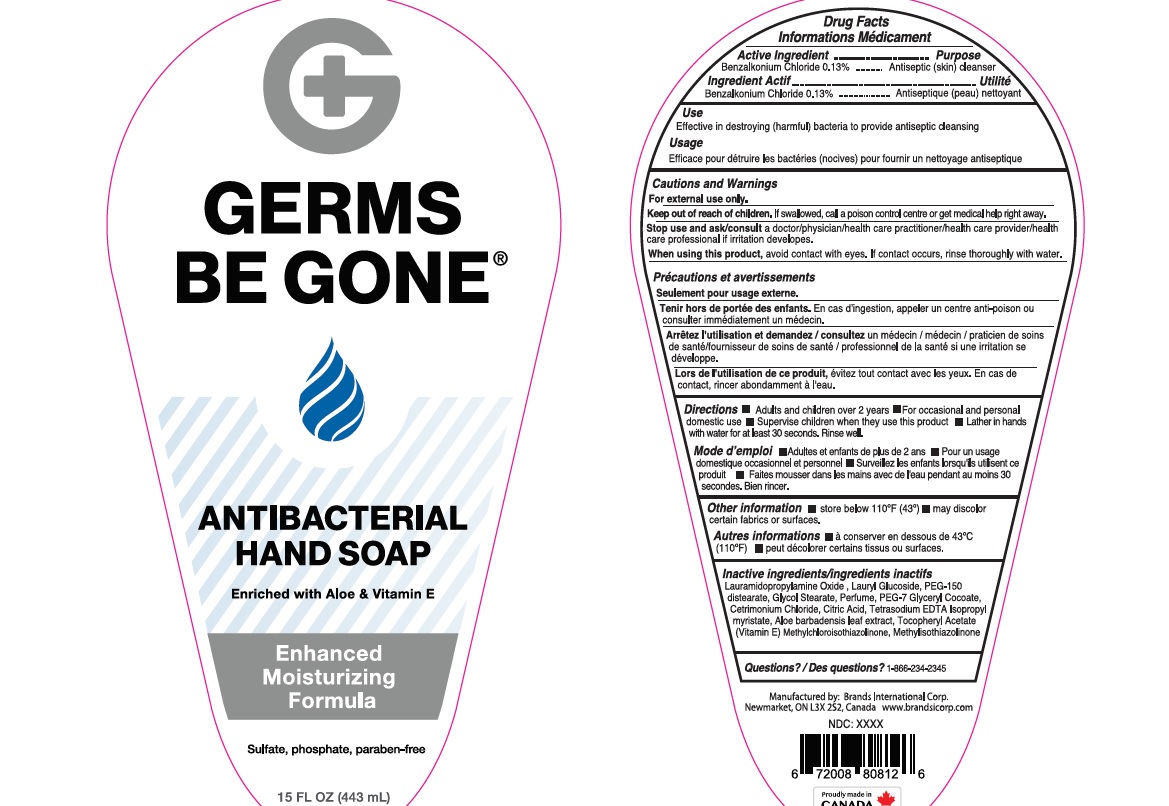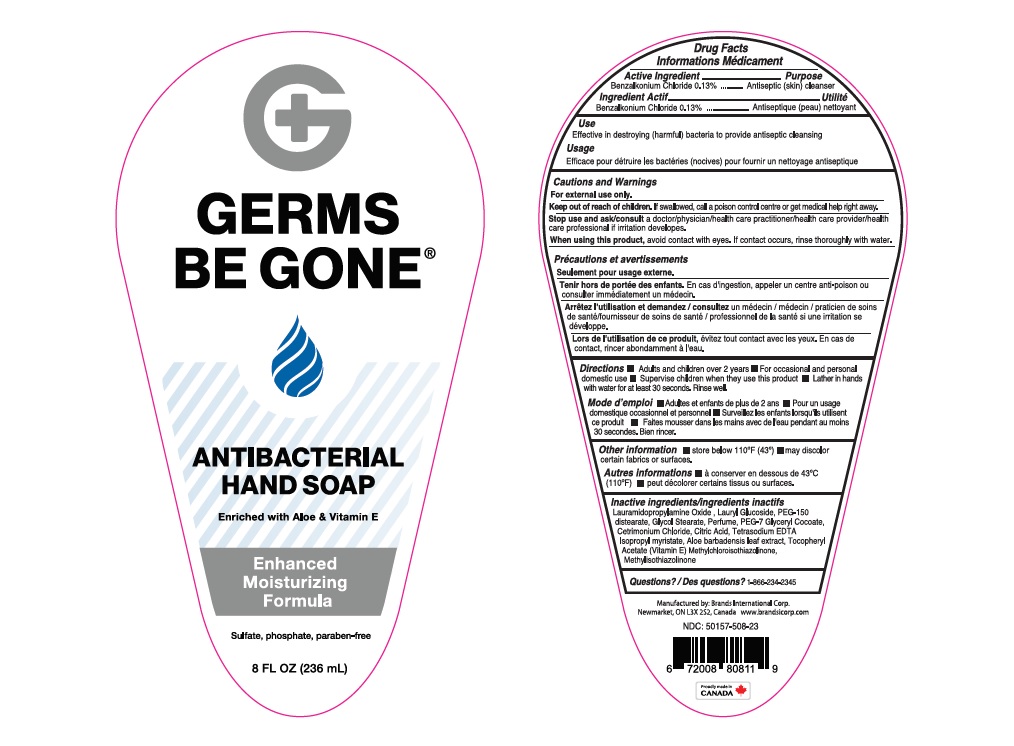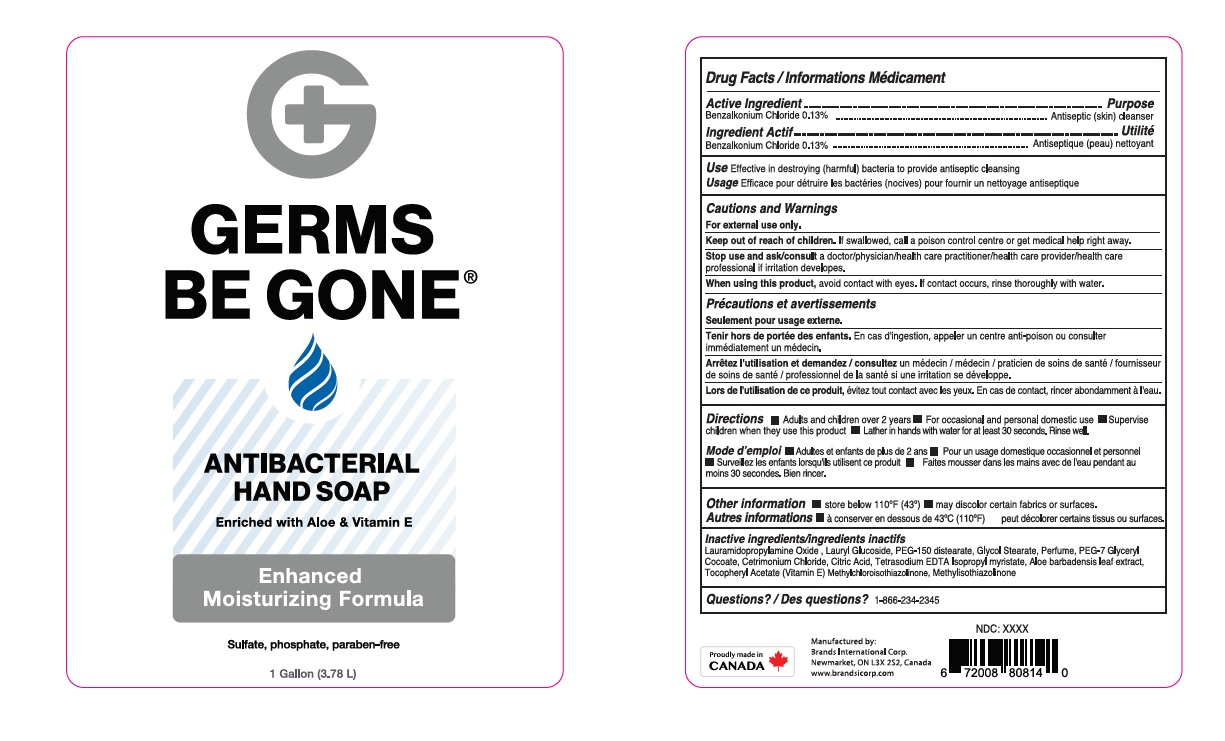 DRUG LABEL: Antibacterial Moisturizing
NDC: 50157-509 | Form: LIQUID
Manufacturer: Brands International Corporation
Category: otc | Type: HUMAN OTC DRUG LABEL
Date: 20200917

ACTIVE INGREDIENTS: BENZALKONIUM CHLORIDE 1.3 mg/1 mL
INACTIVE INGREDIENTS: CITRIC ACID MONOHYDRATE; CETRIMONIUM CHLORIDE; ISOPROPYL MYRISTATE; GLYCOL STEARATE; LAURAMIDOPROPYLAMINE OXIDE; PEG-7 GLYCERYL COCOATE; DITETRACYCLINE TETRASODIUM EDETATE; METHYLCHLOROISOTHIAZOLINONE; METHYLISOTHIAZOLINONE; .ALPHA.-TOCOPHEROL ACETATE; ALOE VERA LEAF; PEG-150 DISTEARATE; LAURYL GLUCOSIDE

Germs be Gone Antibacterial Hand Soap

ACTIVE INGREDIENT

Benzalkonium Chloride - 0.13%

Purpose - Antiseptic Skin cleanser

INDICATIONS AND USAGE

Effective in destroying (harmful) bacteria to provide antiseptic cleansing

Warnings For external use only

Stop use and ask a doctor if irritation or redness develops

When using this product

- do not get it into eyes. If contact occurs, rinse eye thoroughly with water

Keep out of reach of children If swallowed get medical help or contact a Poison Control Center right away

Directions

- wet hands
- apply palmful to hands
- scrub thoroughly
- rinse
- For occasional and personal domestic use
- Supervise children when they use this product.

INACTIVE INGREDIENT

Lauramidopropylamine oxide, Lauryl Glucoside, PEG-150 distearate, Glycol Stearate, Perfume, PEG-7 glycerly cocoate, Cetrimonium Chloride, Citric Acid, Glycerin, Tetrasodium EDTA, Methylchloroisothiazolinone, Methylisothiazolinone, Isopropyl myristate, Tocopheryl Acetate.

OTHER SAFETY INFORMATION

- Store below 110 F (43)
- May discolor certain fabrics or surfaces.